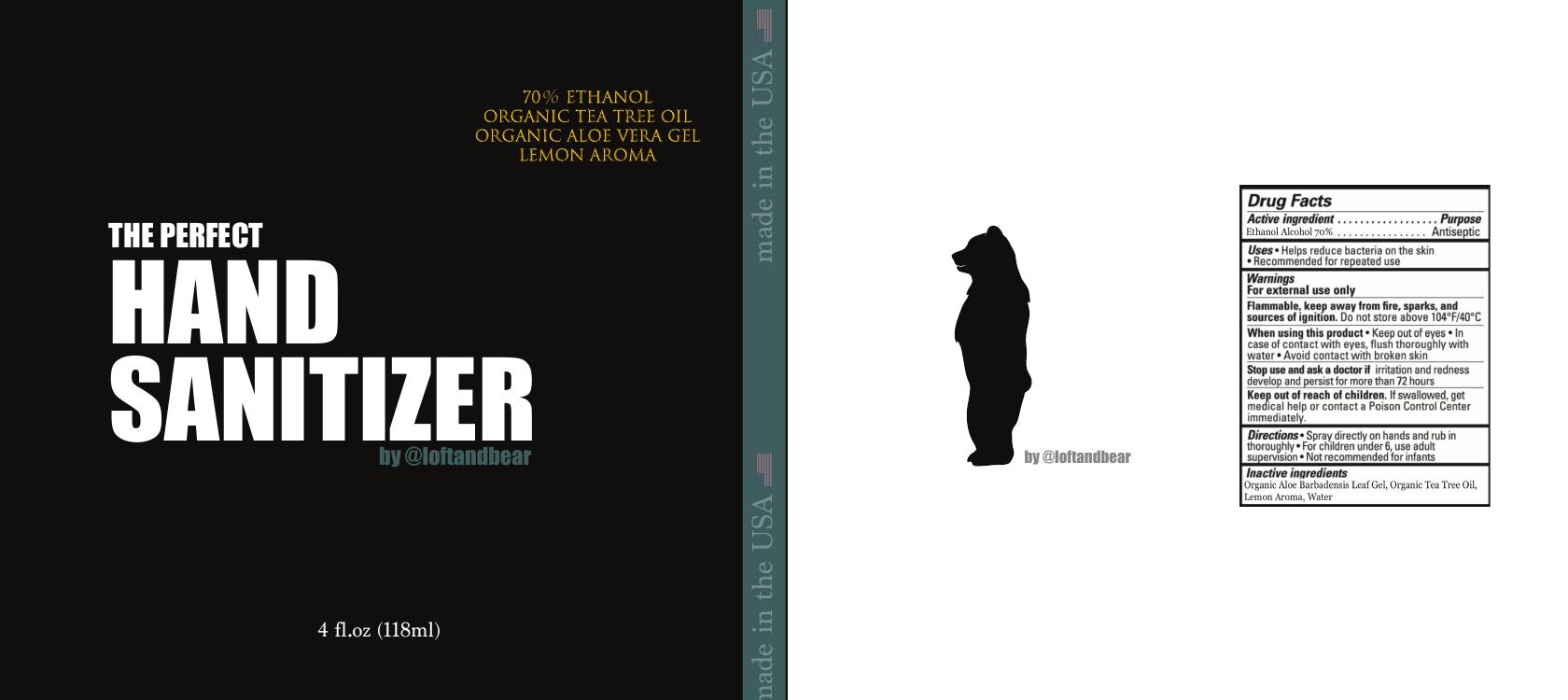 DRUG LABEL: Loft and Bear Hand Wash 4 oz. with Ethanol Alcohol
NDC: 77179-7004 | Form: LIQUID
Manufacturer: Y. SA, INC
Category: otc | Type: HUMAN OTC DRUG LABEL
Date: 20200608

ACTIVE INGREDIENTS: ALCOHOL 118.3 mL/118.3 mL
INACTIVE INGREDIENTS: WATER 118.3 mL/118.3 mL; LEMON OIL 118.3 mL/118.3 mL; TEA TREE OIL 118.3 mL/118.3 mL

Loft and Bear Hand Wash with Ethanol Alcohol

This is a hand sanitizer. f Certain Alcohol-Based Hand Sanitizer Products During the Public Health Emergency (CoViD-19); Guidance for Industry.

The hand sanitizer is manufactured using:

1. Alcohol (ethanol) (USP or Food Chemical Codex (FCC) grade) (70%, volume/volume (v/v)) in an aqueous solution denatured according to Alcohol and Tobacco Tax and Trade Bureau regulations in 27 CFR part 20.
2. Tea Tree Oil (0.125% v/v).
3. Aloe Vera Leaf (0.1% v/v).
4. Lemon Oil (0.0625% v/v).
5. Sterile distilled water or boiled cold water.

Active Ingredient(s)

Alcohol 70% v/v. Purpose: Antiseptic

Purpose

Antiseptic, Hand Sanitizer

Use

Hand Sanitizer to help reduce bacteria that potentially can cause disease. For use when soap and water are not available.

Warnings

For external use only. Flammable. Keep away from heat or flame

Do not use

- in children less than 2 months of age
- on open skin wounds

When using this product keep out of eyes, ears, and mouth. In case of contact with eyes, rinse eyes thoroughly with water.
Stop use and ask a doctor if irritation or rash occurs. These may be signs of a serious condition.
Keep out of reach of children. If swallowed, get medical help or contact a Poison Control Center right away.

Stop use and ask a doctor if irritation or rash occurs. These may be signs of a serious condition.

Keep out of reach of children. If swallowed, get medical help or contact a Poison Control Center right away.

Directions

- Place enough product on hands to cover all surfaces. Rub hands together until dry.
- Supervise children under 6 years of age when using this product to avoid swallowing.

Other information

- Store between 15-30C (59-86F)
- Avoid freezing and excessive heat above 40C (104F)

Inactive ingredients

aloe vera leaf, tea tree oil, lemon oil, purified water USP

Package Label - Principal Display Panel

118.3 mL NDC: 77179-7004-3